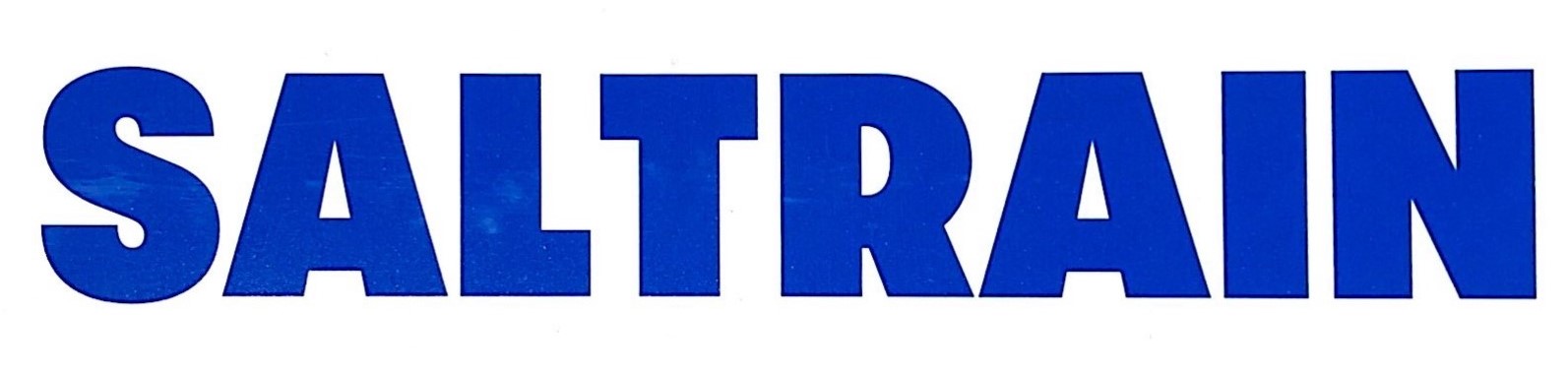 DRUG LABEL: SALTRAIN TOOTH
NDC: 74724-0021 | Form: PASTE
Manufacturer: K.Boeun Pharmaceutical Co.,Ltd.
Category: otc | Type: HUMAN OTC DRUG LABEL
Date: 20201111

ACTIVE INGREDIENTS: SODIUM MONOFLUOROPHOSPHATE 0.4 g/100 g
INACTIVE INGREDIENTS: XYLITOL; WATER; AMINOCAPROIC ACID; SILICON DIOXIDE

ACTIVE INGREDIENT

Sodium Monofluorophosphate

PURPOSE

For dental care

Keep out of reach of children

INDICATIONS AND USAGE

Apply an appropriate amount to your toothbrush and brush your teeth by brushing

Keep out of reach of children under 6 years old.

If more than used for brushing is accidentally swallowed, get medical help or contact a Poison Control Center right away.

INACTIVE INGREDIENT

Precipitated Calcium Carbonate, Dibasic Calcium Phosphate, Aminocaproic Acid, Aluminium Chlorohydroxy Allantoinate, D-Sorbitol Solution, Concentrated Glycerin, Polyethylene Glycol 1500, Xanthangum, Sodium Cocoyl Glutamate, Silicon Dioxide, Titanium Oxide, Enzymatically Modified Stevia, Xylitol, Sodium Chloride, Ascorbic Acid, Mentha Oil, l-Menthol, Spearmint Oil, Water

DOSAGE AND ADMINISTRATION

For dental use only